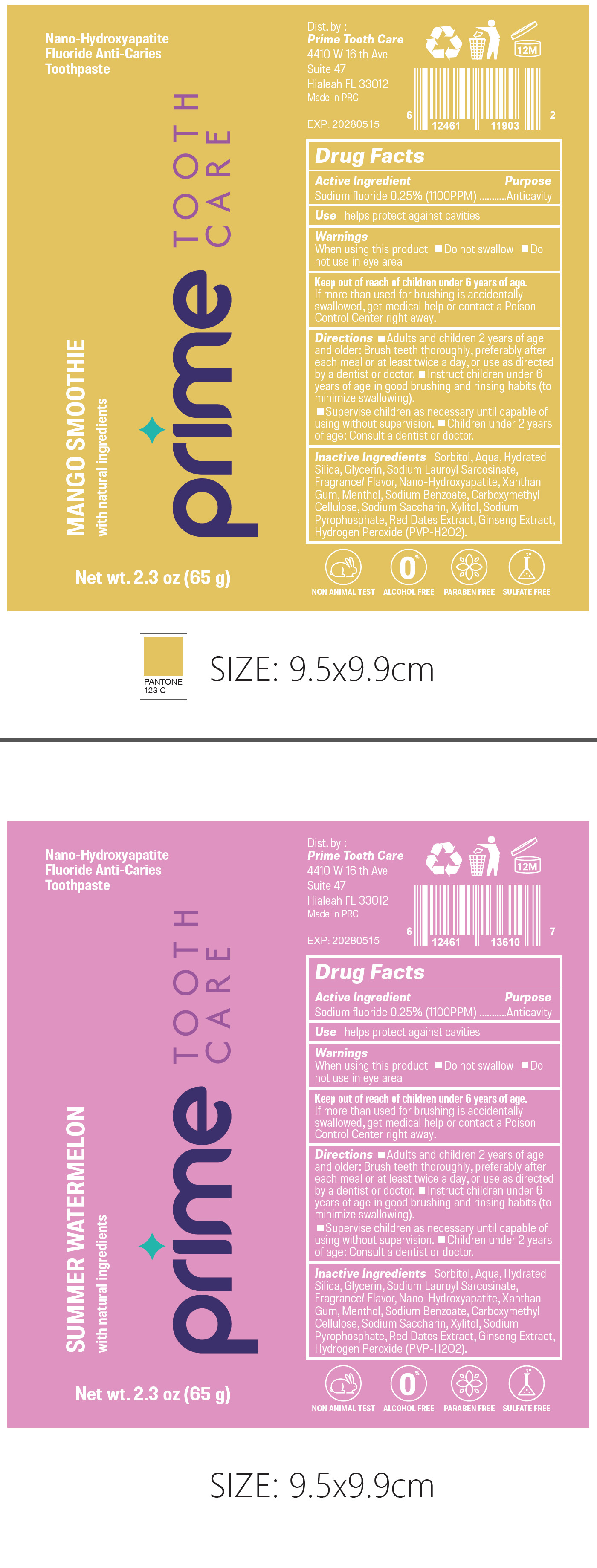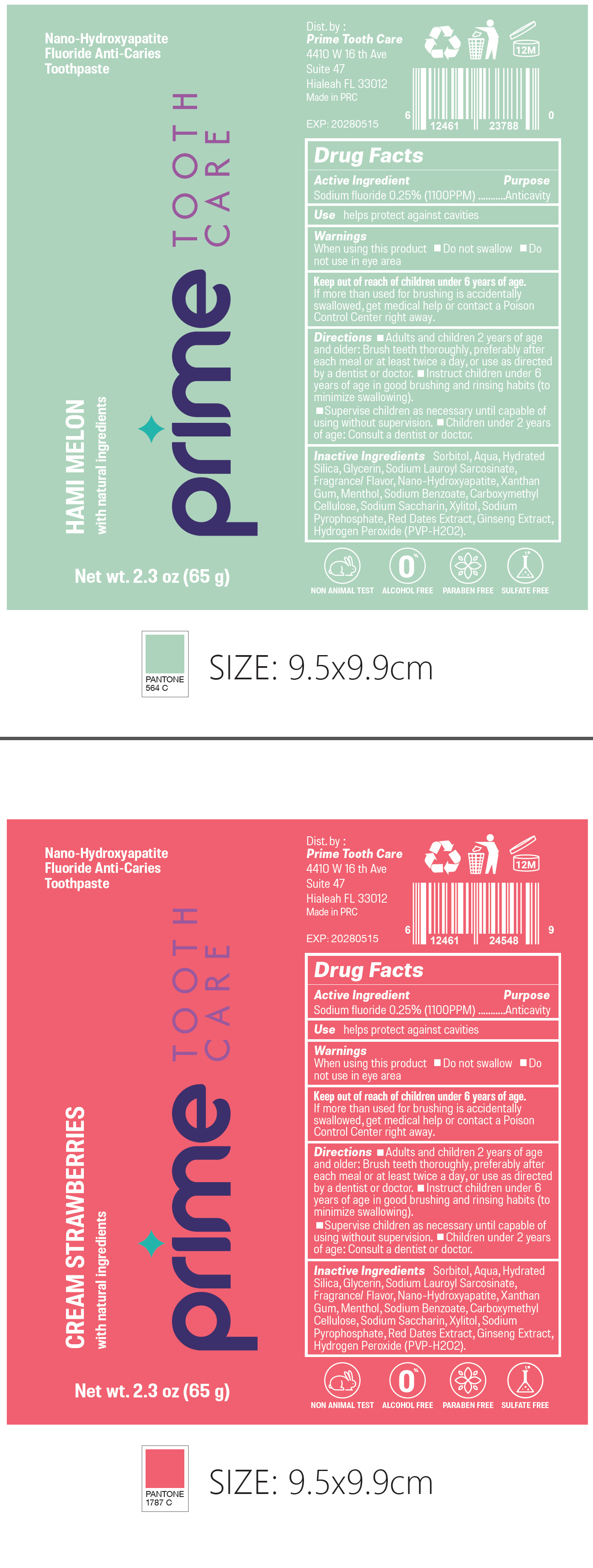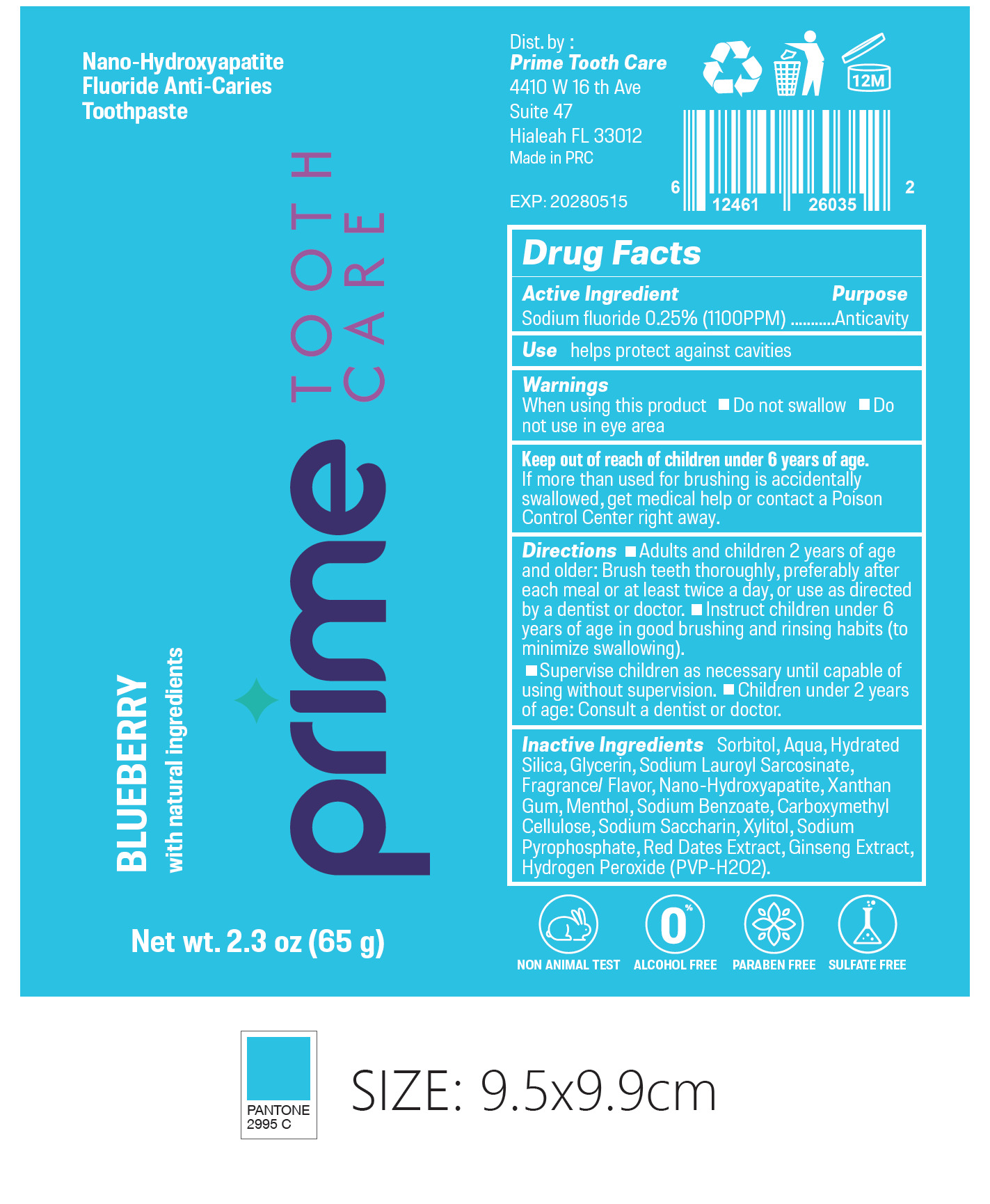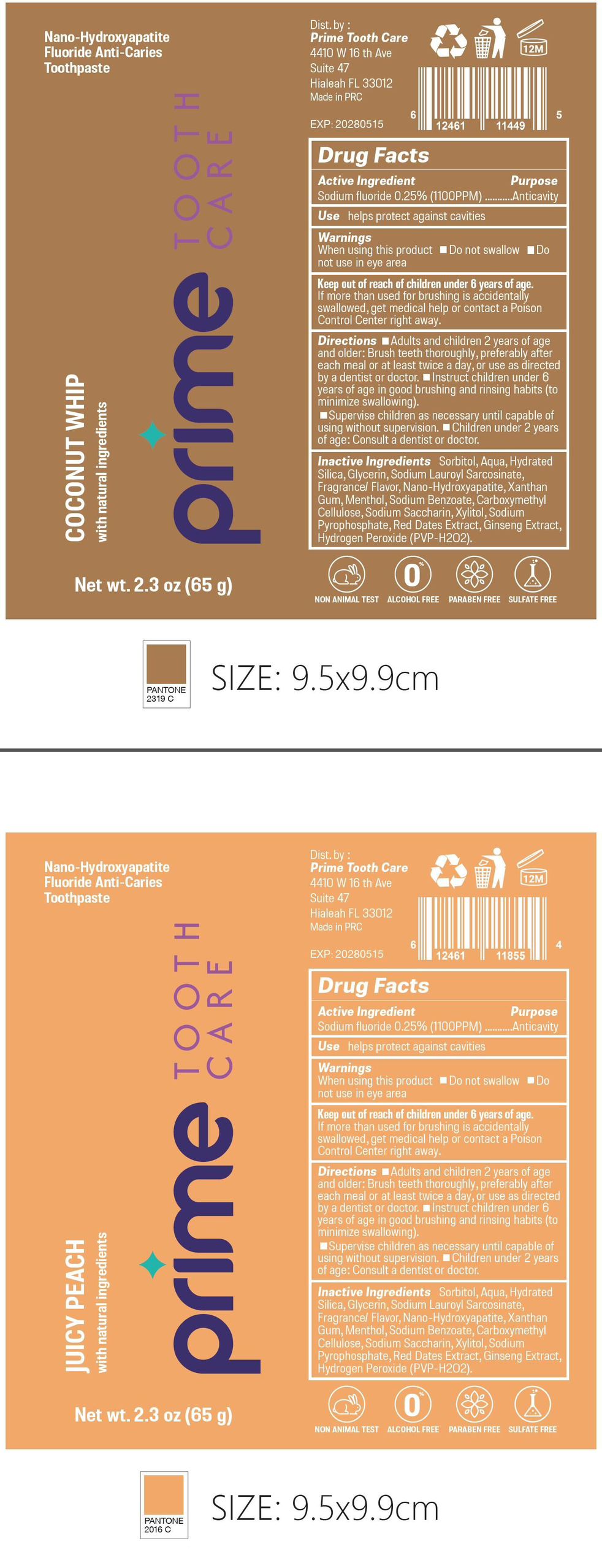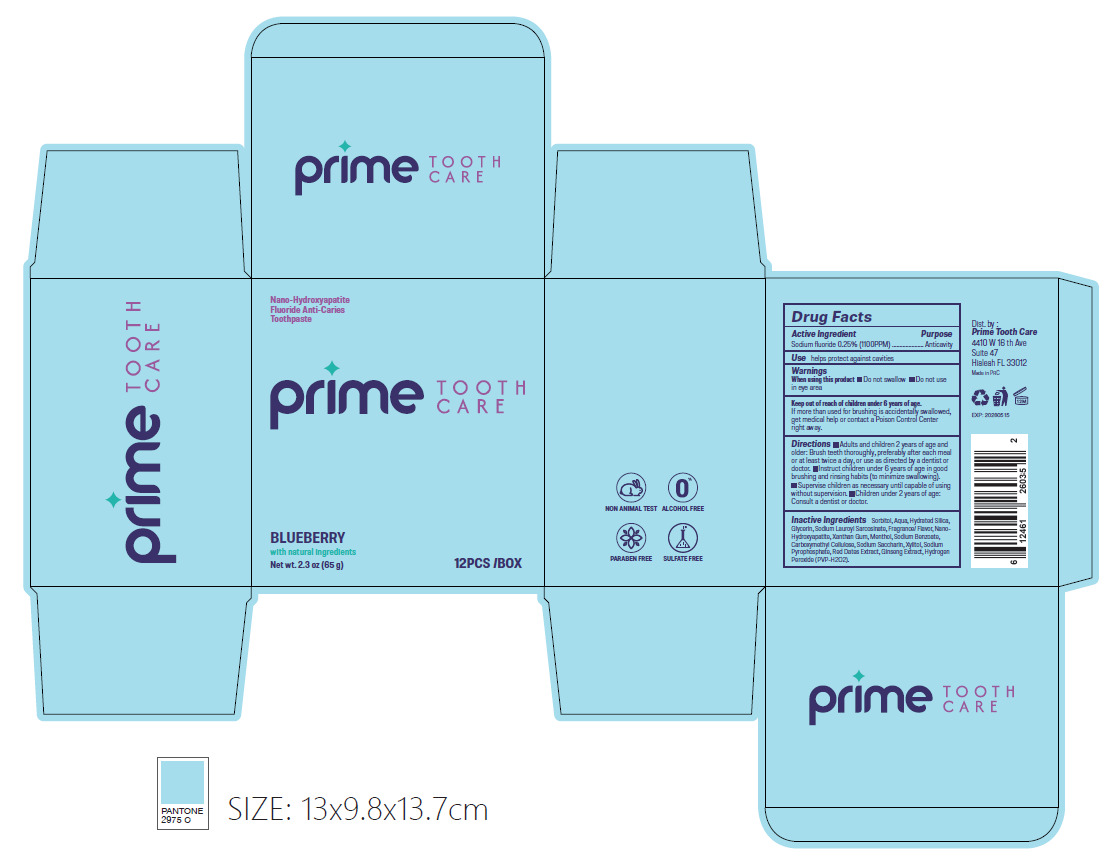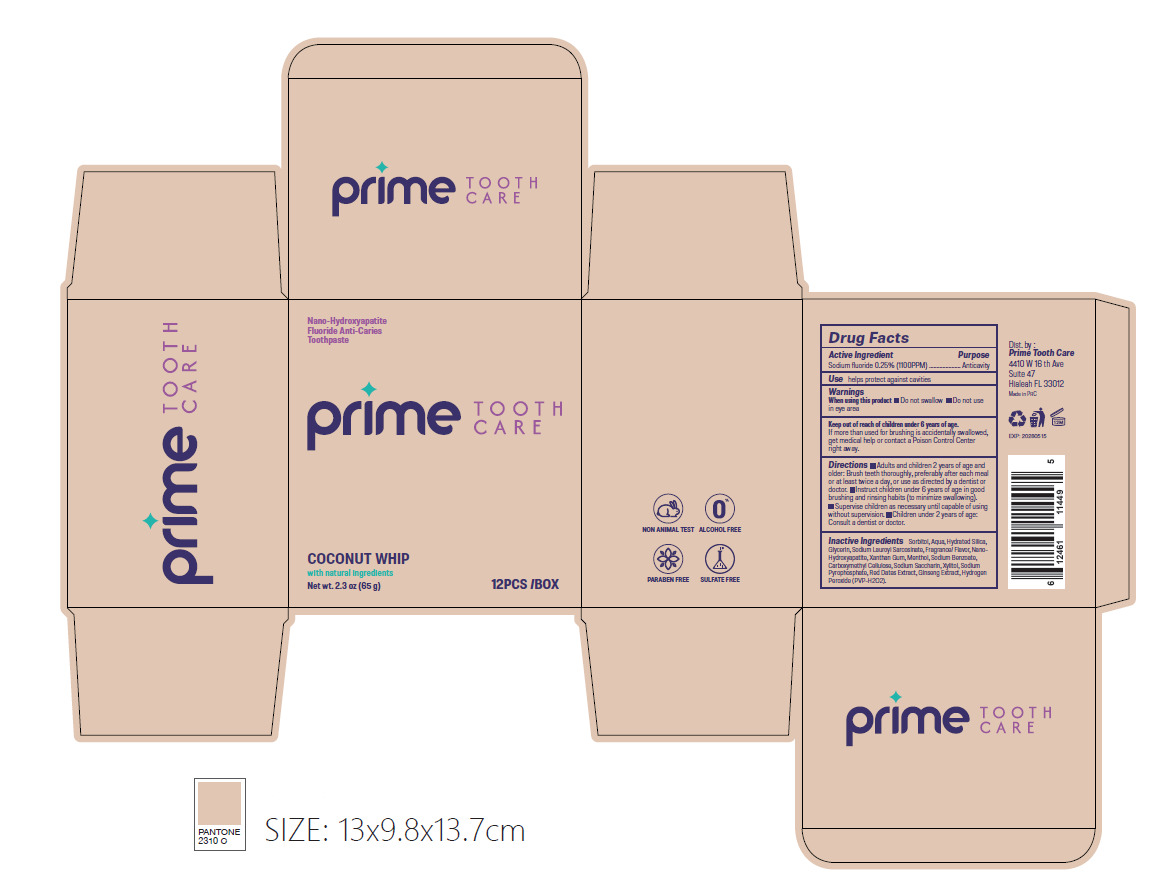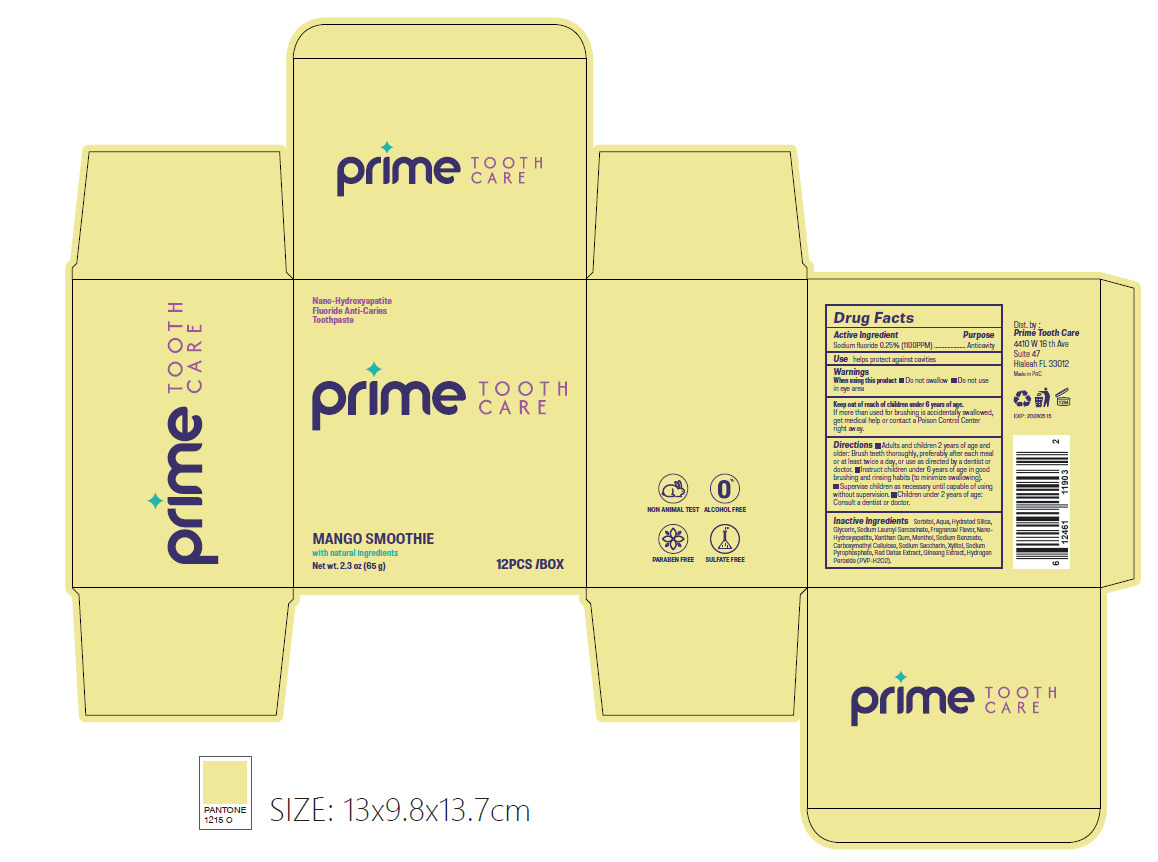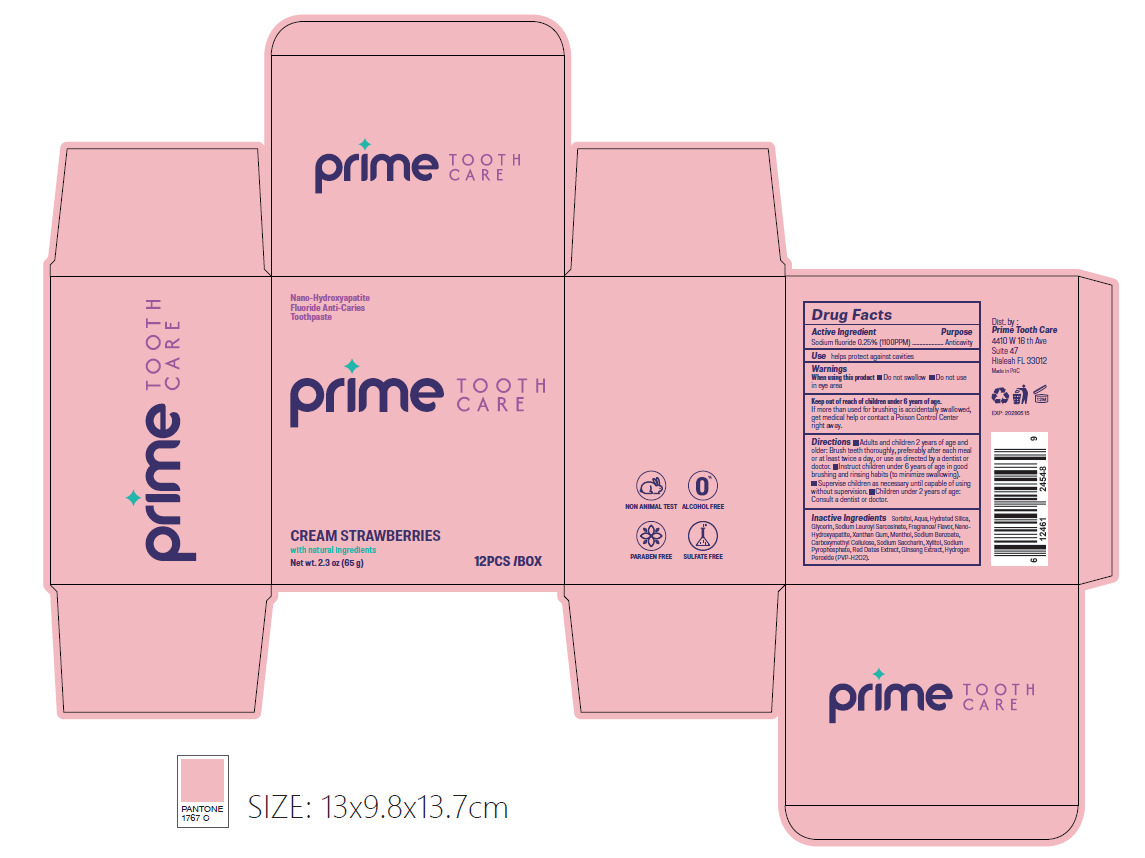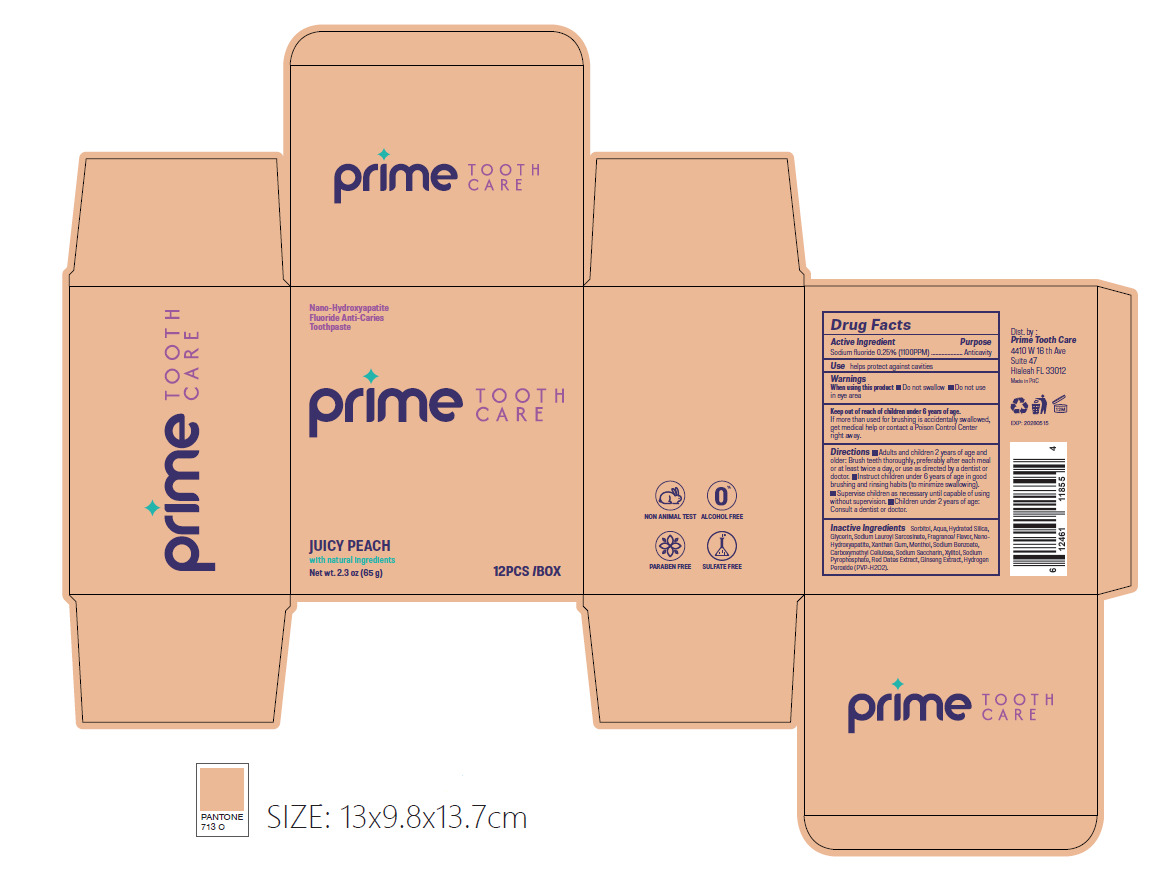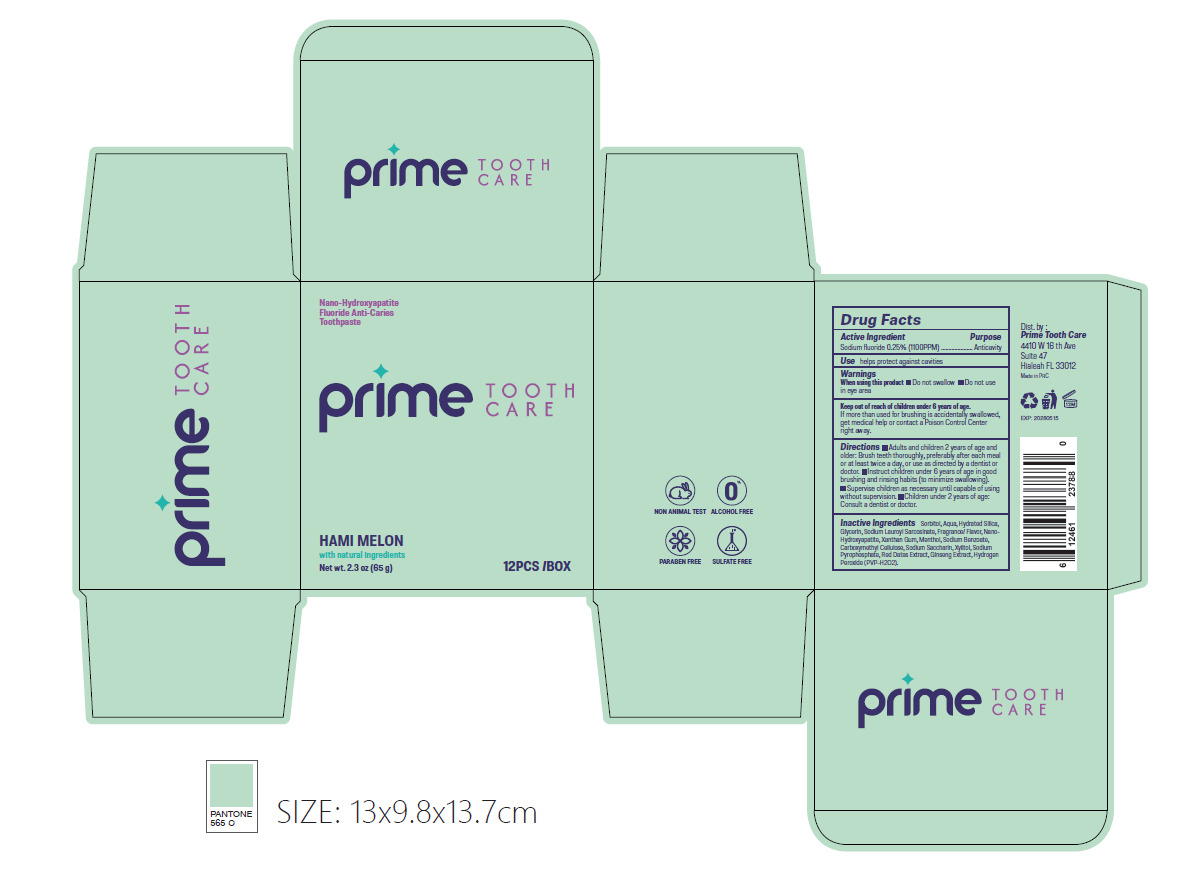 DRUG LABEL: Fluoride Anti Caries 65g Coconut Whip Juicy Peach Mango Smoothie Summer Watermelon Hami Melom Cream Strawberries Blueberry
NDC: 85215-002 | Form: OINTMENT
Manufacturer: WORLD DENTISTS ASSOCIATION AMERICA LIMITED
Category: otc | Type: HUMAN OTC DRUG LABEL
Date: 20250518

ACTIVE INGREDIENTS: SODIUM FLUORIDE 0.25 g/100 g
INACTIVE INGREDIENTS: XANTHAN GUM; SODIUM BENZOATE; GLYCERIN; XYLITOL; SODIUM SACCHARIN; SODIUM LAUROYL SARCOSINATE; SODIUM PYROPHOSPHATE; MENTHOL; SORBITOL; AQUA; SILICA; HYDROGEN PEROXIDE; CARBOXYMETHYLCELLULOSE; SCHISANDRA CHINENSIS FRUIT; ASIAN GINSENG

85215-002

Active Ingredient(s)

Sodium fluoride 0.25% (100PPM)

Purpose

Anticavity

Use

Use helps protect against cavities

Warnings

When using this product

Do not swallow

Do not use in eye area

Do not use in eye area

When using this product

Do not swallow

When using this product keep out of eyes

KEEP OUT OF REACH OF CHILDREN

Keep out of Teach of children under 6 years of age.
If more than used for brushing is accidentally
swallowed, get medical help or contact a Poison
Control Center right away.

Directions

Directions ■Adults and children 2 years of age and older: Brush teeth thoroughly, preferably after
each meal or at east twice a day, or use as directed by a dentist or doctor.

■Instruct children under 6 years of age in good brushing and rinsing habits (to minimize swallowing).
■Supervise children as necessary until capable of using without supervision.

■Children under 2 years of age: Consult a dentist or doctor.

Other information

Store in a cool and shady place

Inactive ingredients

Sorbitol, Aqua, Hydrated Silica, Glycerin, Sodium Lauroy| Sarcosinate, Fragrancel Flavor, Nano-Hydroxyapatite, Xanthan
Gum, Menthol, Sodium Benzoate, CarboxymethyI Cellulose, Sodium Saccharin, Xylitol, Sodium Pyrophosphate, Red Dates Extract, Ginseng Extract, Hydrogen Peroxide (PVP-H202).

Package Label - Principal Display Panel

、